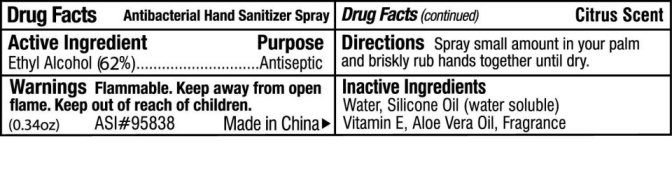 DRUG LABEL: Antibacterial Hand Sanitizer Spray
NDC: 49701-2000 | Form: SPRAY
Manufacturer: The Webb Company 
Category: otc | Type: HUMAN OTC DRUG LABEL
Date: 20091117

ACTIVE INGREDIENTS: ALCOHOL 62 mL/100 mL
INACTIVE INGREDIENTS: WATER; ALPHA-TOCOPHEROL; ALOE VERA LEAF

Antibacterial Hand Sanitizer Spray Citrus Scent

Active Ingredient Purpose

Ethyl Alcohol (62 percent) Antiseptic

Warnings Flammable.

Keep away from open flame.

Keep out of reach of children.

DOSAGE AND ADMINISTRATION

Directions: Spray small amount in your palm and briskly rub hands together until dry.

Inactive Ingredients

water, silicone oil (water soluble) vitamin E, Aloe vera oil, fragrance

DESCRIPTION

(0.34 oz) Made in China